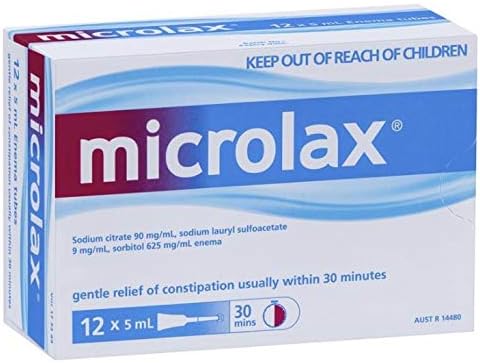 DRUG LABEL: Microlax Enema
NDC: 84177-0020 | Form: ENEMA
Manufacturer: MEDIA NETWORKS SYDNEY PTY LIMITED
Category: otc | Type: HUMAN OTC DRUG LABEL
Date: 20240324

ACTIVE INGREDIENTS: SORBITOL 625 mg/1 g
INACTIVE INGREDIENTS: TRISODIUM CITRATE DIHYDRATE 90 mg/1 g; SODIUM LAURYL SULFOACETATE 9 mg/1 g; GLYCEROL FORMAL; WATER; SORBIC ACID

DOSAGE AND ADMINISTRATION

Dosage Form Enema Route of Administration Rectal Visual Identification A colourless, opalescent and viscous preparation.

No Warnings included on Record

INACTIVE INGREDIENT

glycerol purified water sorbic acid

INDICATIONS AND USAGE

Permitted Indications No Permitted Indications included on Record Indication Requirements No Indication Requirements included on Record

keep out of reach of children

PURPOSE

Single Medicine Product Specific Indications Rectal constipation, faecal incontinence; preparation for X-ray examination and rectoscopy

Active Ingredients

sodium citrate dihydrate 90 mg/mL

sodium lauryl sulfoacetate 9 mg/mL

sorbitol 625 mg/mL

PACKAGE LABEL

Microlax Enema 5mlx12